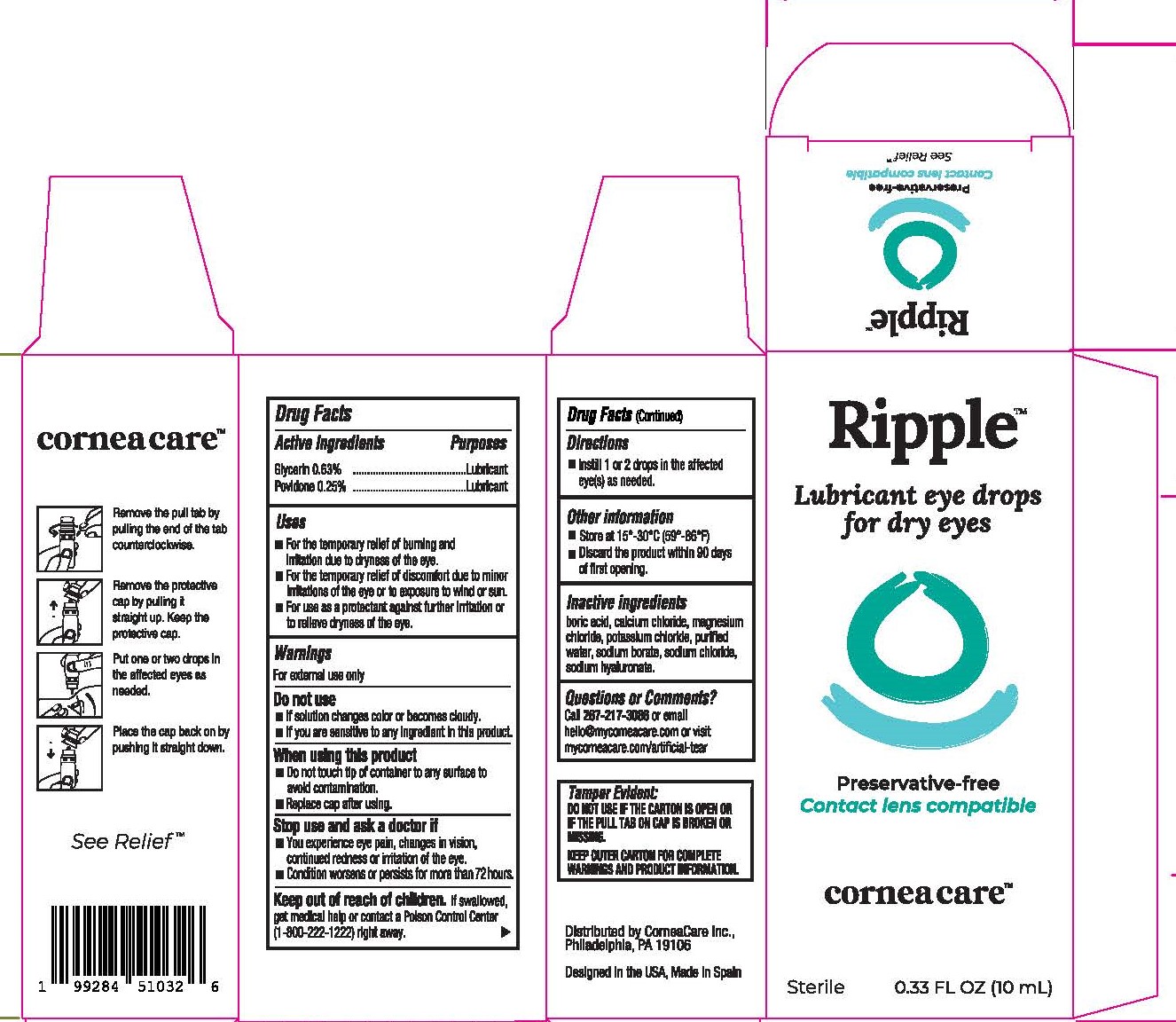 DRUG LABEL: Ripple
NDC: 82875-003 | Form: SOLUTION/ DROPS
Manufacturer: CorneaCare Inc
Category: otc | Type: HUMAN OTC DRUG LABEL
Date: 20250802

ACTIVE INGREDIENTS: GLYCERIN 0.63 g/100 mL; POVIDONE 0.25 g/100 mL
INACTIVE INGREDIENTS: MAGNESIUM CHLORIDE; SODIUM BORATE; HYALURONATE SODIUM; BORIC ACID; WATER; CALCIUM CHLORIDE; POTASSIUM CHLORIDE; SODIUM CHLORIDE

Ripple Eye Lubricant Drops

Keep out of reach of children. If swallowed get medical help or contact a Poison Control Center
(1-800-222-1222)right away. ►

PURPOSE

Eye Lubricant

Warnings
For external use only
Do not use
■If solution changes color or becomes cloudy.
■lf you are sensitive to any ingredient in this product.
When using this product
■Do not touch tip of container to any surface to
avoid contamination.
■Replace cap after using.
Stop use and ask a doctor if
■You experience eye pain, changes in vision,
continued redness or irritation of the eye.
■ Condition worsens or persists for more than 72 hours.

Uses

• For temporary relief of burning and irritation due to dryness of the eye.

• For the temporary relief of discomfort due to minor irritations of the eye or to exposure to wind or sun

• For use as a protectant against irritation or to relieve dryness of the eye.

DOSAGE AND ADMINISTRATION

Instill 1 or 2 drops in the eye(s) as needed.

ACTIVE INGREDIENT

Glycerin 0.63%
Povidone 0.25%

Inactive ingredients
boric acid, calcium chloride, magnesium chloride, potassium chloride ,purified water, sodium borate, sodium chloride, sodium hyaluronate.